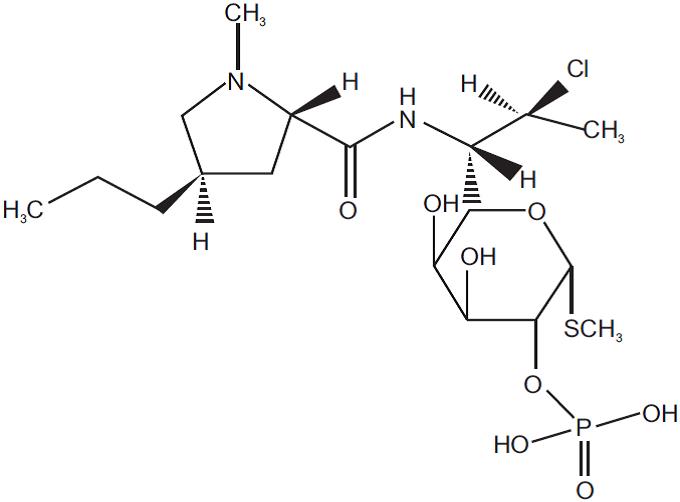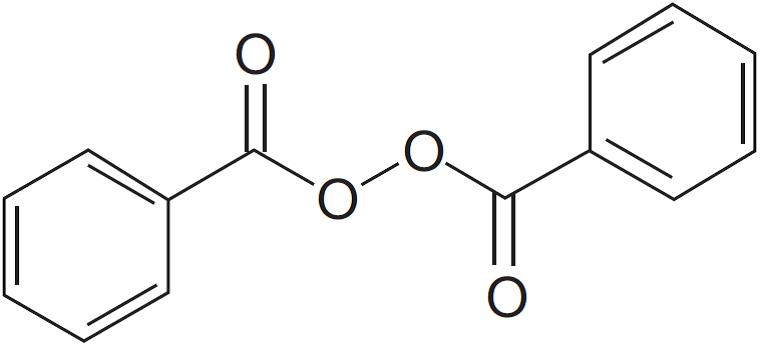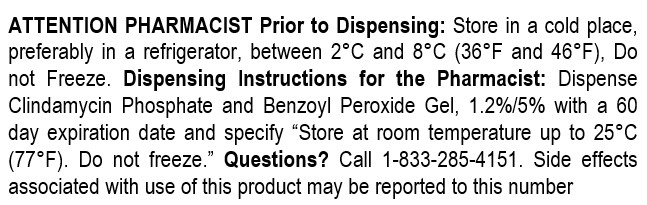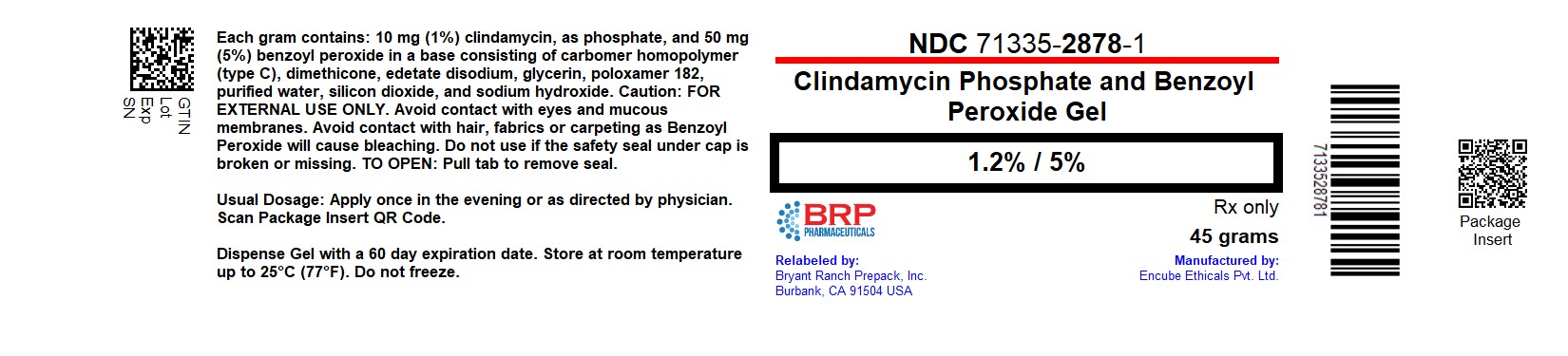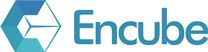 DRUG LABEL: CLINDAMYCIN PHOSPHATE AND BENZOYL PEROXIDE
NDC: 71335-2878 | Form: GEL
Manufacturer: Bryant Ranch Prepack
Category: prescription | Type: HUMAN PRESCRIPTION DRUG LABEL
Date: 20251022

ACTIVE INGREDIENTS: CLINDAMYCIN PHOSPHATE 10 mg/1 g; BENZOYL PEROXIDE 50 mg/1 g
INACTIVE INGREDIENTS: CARBOMER HOMOPOLYMER TYPE C (ALLYL PENTAERYTHRITOL CROSSLINKED); EDETATE DISODIUM; DIMETHICONE; GLYCERIN; SILICON DIOXIDE; POLOXAMER 182; WATER; SODIUM HYDROXIDE

HIGHLIGHTS OF PRESCRIBING INFORMATION

These highlights do not include all the information needed to use Clindamycin Phosphate and Benzoyl Peroxide Gel, 1.2%/5% safely and effectively. See full prescribing information for Clindamycin Phosphate and Benzoyl Peroxide Gel, 1.2%/5%.
Clindamycin Phosphate and Benzoyl Peroxide Gel, 1.2% / 5%,
for topical use
Initial U.S. Approval: 2000

1 INDICATIONS AND USAGE

Clindamycin Phosphate and Benzoyl Peroxide Gel, 1.2%/5% is a combination of clindamycin phosphate (a lincosamide antibacterial) and benzoyl peroxide indicated for the topical treatment of inflammatory acne vulgaris. (1.1)

Limitation of Use:

Clindamycin Phosphate and Benzoyl Peroxide Gel, 1.2%/5% has not been demonstrated to have any additional benefit when compared with benzoyl peroxide alone in the same vehicle when used for the treatment of non-inflammatory acne. (1.2)

2 DOSAGE AND ADMINISTRATION

- Apply a thin layer of Clindamycin Phosphate and Benzoyl Peroxide Gel, 1.2%/5% to the face once daily, in the evening. (2)
- Not for oral, ophthalmic, or intravaginal use. (2)

3 DOSAGE FORMS AND STRENGTHS

Gel, 1.2%/5%: Each gram of Clindamycin Phosphate and Benzoyl Peroxide Gel, 1.2%/5% contains 12 mg clindamycin phosphate (equivalent to 10 mg of clindamycin) and 50 mg benzoyl peroxide. (3)

4 CONTRAINDICATIONS

Clindamycin Phosphate and Benzoyl Peroxide Gel, 1.2%/5% is contraindicated in:

- Patients who have demonstrated hypersensitivity (e.g., anaphylaxis) to clindamycin, benzoyl peroxide, any components of the formulation, or lincomycin. (4)
- Patients with a history of regional enteritis, ulcerative colitis, or antibiotic-associated colitis (including pseudomembranous colitis). (4)

5 WARNINGS AND PRECAUTIONS

- Colitis: Clindamycin can cause severe colitis, which may result in death. Diarrhea, bloody diarrhea, and colitis (including pseudomembranous colitis) have been reported with the use of clindamycin. Clindamycin Phosphate and Benzoyl Peroxide Gel, 1.2%/5% should be discontinued if significant diarrhea occurs. (5.1)
- Ultraviolet light and environmental exposure (including use of tanning beds or sun lamps): Minimize sun exposure following drug application. (5.2)

6 ADVERSE REACTIONS

The most common local adverse reactions (≥5%) are erythema, peeling, dryness and burning. (6.1)

To report SUSPECTED ADVERSE REACTIONS, contact Encube Ethicals Private Limited at 1-833-285-4151 or FDA at 1-800-FDA-1088 or www.fda.gov/medwatch.

7 DRUG INTERACTIONS

- Clindamycin Phosphate and Benzoyl Peroxide Gel, 1.2%/5% should not be used in combination with erythromycin-containing products because of its clindamycin component. (7.1)

FULL PRESCRIBING INFORMATION

1 INDICATIONS AND USAGE

1.1 Indication

Clindamycin Phosphate and Benzoyl Peroxide Gel, 1.2%/5% is indicated for the topical treatment of inflammatory acne vulgaris in patients 12 years and older.

1.2 Limitations of Use

Clindamycin Phosphate and Benzoyl Peroxide Gel, 1.2%/5% has not been demonstrated to have any additional benefit when compared with benzoyl peroxide alone in the same vehicle when used for the treatment of non-inflammatory acne.

2 DOSAGE AND ADMINISTRATION

Apply a thin layer of Clindamycin Phosphate and Benzoyl Peroxide Gel, 1.2%/5% to the face once daily, in the evening or as directed by the physician. The skin should be gently washed, rinsed with warm water, and patted dry before applying Clindamycin Phosphate and Benzoyl Peroxide Gel, 1.2%/5%. Avoid the eyes, mouth, lips, mucous membranes, or areas of broken skin.

Clindamycin Phosphate and Benzoyl Peroxide Gel, 1.2%/5% is not for oral, ophthalmic, or intravaginal use.

3 DOSAGE FORMS AND STRENGTHS

Gel, 1.2%/5%

Clindamycin Phosphate and Benzoyl Peroxide Gel, 1.2%/5% is a white to slightly yellow, opaque gel. Each gram of Clindamycin Phosphate and Benzoyl Peroxide Gel, 1.2%/5% contains 12 mg clindamycin phosphate (equivalent to 10 mg of clindamycin) and 50 mg benzoyl peroxide.

4 CONTRAINDICATIONS

4.1 Hypersensitivity

Clindamycin Phosphate and Benzoyl Peroxide Gel, 1.2%/5% is contraindicated in those individuals who have shown hypersensitivity to clindamycin, benzoyl peroxide, any components of the formulation, or lincomycin. Anaphylaxis, as well as allergic reactions leading to hospitalization, has been reported in postmarketing use with Clindamycin Phosphate and Benzoyl Peroxide Gel, 1.2%/5%. [See Adverse Reactions (6.2).]

4.2 Colitis/Enteritis

Clindamycin Phosphate and Benzoyl Peroxide Gel, 1.2%/5% is contraindicated in those individuals with a history of regional enteritis, ulcerative colitis, pseudomembranous colitis, or antibiotic-associated colitis [see Warnings and Precautions (5.1)].

5 WARNINGS AND PRECAUTIONS

5.1 Colitis

Systemic absorption of clindamycin has been demonstrated following topical use of clindamycin. Diarrhea, bloody diarrhea, and colitis (including pseudomembranous colitis) have been reported with the use of topical and systemic clindamycin. If significant diarrhea occurs, Clindamycin Phosphate and Benzoyl Peroxide Gel, 1.2%/5% should be discontinued.

Severe colitis has occurred following oral and parenteral administration of clindamycin with an onset of up to several weeks following cessation of therapy. Antiperistaltic agents such as opiates and diphenoxylate with atropine may prolong and/or worsen severe colitis. Severe colitis may result in death.

Studies indicate a toxin(s) produced by Clostridia is one primary cause of antibiotic-associated colitis. The colitis is usually characterized by severe persistent diarrhea and severe abdominal cramps and may be associated with the passage of blood and mucus. Stool cultures for Clostridium difficile and stool assay for C. difficile toxin may be helpful diagnostically.

5.2 Ultraviolet Light and Environmental Exposure

Benzoyl peroxide, a component of Clindamycin Phosphate and Benzoyl Peroxide Gel, 1.2%/5%, may cause increased sensitivity to sunlight. Minimize sun exposure (including use of tanning beds or sun lamps) following drug application. [See Nonclinical Toxicology (13.1.)] Patients who may be required to have considerable sun exposure due to occupation and those with inherent sensitivity to the sun should exercise particular caution.

6 ADVERSE REACTIONS

The following adverse reaction is described in more detail in the Warnings and Precautions section of the label:

- Colitis [see Warnings and Precautions (5.1)].

6.1 Clinical Trials Experience

Because clinical trials are conducted under widely varying conditions, adverse reaction rates observed in the clinical trials of a drug cannot be directly compared with rates in the clinical trials of another drug and may not reflect the rates observed in practice.

During clinical trials, 397 subjects used Clindamycin Phosphate and Benzoyl Peroxide Gel, 1.2%/5% once daily for 11 weeks for the treatment of moderate to moderately severe facial acne vulgaris. All subjects were graded for facial local skin reactions (erythema, peeling, burning, and dryness) on the following scale: 0 = absent, 1 = mild, 2 = moderate, and 3 = severe. The percentage of subjects that had symptoms present before treatment (at baseline) and during treatment is presented in Table 1.

Table 1. Local Skin Reactions with Use of Clindamycin Phosphate and Benzoyl Peroxide Gel, 1.2%/5%

Combined Results from Five Trials (n = 397)

 | % of Subjects Using Clindamycin Phosphate and Benzoyl Peroxide Gel, 1.2%/5% with Symptom Present
 | Before Treatment (Baseline) |  |  | During Treatment
Symptom | Mild | Moderate | Severe | Mild | Moderate | Severe
Erythema | 28% | 3% | 0 | 26% | 5% | 0
Peeling | 6% | <1% | 0 | 17% | 2% | 0
Burning | 3% | <1% | 0 | 5% | <1% | 0
Dryness | 6% | <1% | 0 | 15% | 1% | 0

(Percentages derived by number of subjects receiving Clindamycin Phosphate and Benzoyl Peroxide Gel, 1.2%/5% with symptom score/number of enrolled subjects receiving Clindamycin Phosphate and Benzoyl Peroxide Gel, 1.2%/5%).

6.2 Postmarketing Experience

The following adverse reactions have been identified during postapproval use of Clindamycin Phosphate and Benzoyl Peroxide Gel, 1.2%/5%. Because these reactions are reported voluntarily from a population of uncertain size, it is not always possible to reliably estimate their frequency or establish a causal relationship to drug exposure.

Anaphylaxis, as well as allergic reactions leading to hospitalization, has been reported in postmarketing use with Clindamycin Phosphate and Benzoyl Peroxide Gel, 1.2%/5%.

Urticaria, application site reactions, including discoloration have been reported.

7 DRUG INTERACTIONS

7.1 Erythromycin

Avoid using Clindamycin Phosphate and Benzoyl Peroxide Gel, 1.2%/5% in combination with erythromycin-containing products due to its clindamycin component. In vitro studies have shown antagonism between erythromycin and clindamycin. The clinical significance of this in vitro antagonism is not known.

7.2 Concomitant Topical Medications

Concomitant topical acne therapies should be used with caution since a possible cumulative irritancy effect may occur, especially with the use of peeling, desquamating, or abrasive agents. If irritancy or dermatitis occurs, reduce frequency of application or temporarily interrupt treatment and resume once the irritation subsides. Treatment should be discontinued if the irritation persists.

7.3 Neuromuscular Blocking Agents

Clindamycin has been shown to have neuromuscular blocking properties that may enhance the action of other neuromuscular blocking agents. Clindamycin Phosphate and Benzoyl Peroxide Gel, 1.2%/5% should be used with caution in patients receiving such agents.

7.4 Topical Sulfone Products

Use of topical benzoyl-peroxide-containing preparations with topical sulfone products may cause skin and facial hair to temporarily change color (yellow/orange).

8 USE IN SPECIFIC POPULATIONS

8.1 Pregnancy

Pregnancy Category C.

There are no adequate and well-controlled studies in pregnant women treated with Clindamycin Phosphate and Benzoyl Peroxide Gel, 1.2%/5%. Clindamycin Phosphate and Benzoyl Peroxide Gel, 1.2%/5% should be used during pregnancy only if the potential benefit justifies the potential risk to the fetus.

Developmental toxicity studies performed in rats and mice using oral doses of clindamycin up to 600 mg per kg per day (240 and 120 times the amount of clindamycin in the highest recommended adult human dose based on mg per m^2, respectively) or subcutaneous doses of clindamycin up to 250 mg per kg per day (100 and 50 times the amount of clindamycin in the highest recommended adult human dose based on mg per m^2, respectively) revealed no evidence of teratogenicity.

8.3 Nursing Mothers

It is not known whether Clindamycin Phosphate and Benzoyl Peroxide Gel, 1.2%/5% is excreted into human milk after topical application. However, orally and parenterally administered clindamycin has been reported to appear in breast milk. Because of the potential for serious adverse reactions in nursing infants, a decision should be made whether to discontinue nursing or to discontinue the drug, taking into account the importance of the drug to the mother. Because many drugs are excreted in human milk, caution should be exercised when Clindamycin Phosphate and Benzoyl Peroxide Gel, 1.2%/5% is administered to a nursing woman.

8.4 Pediatric Use

Safety and effectiveness of Clindamycin Phosphate and Benzoyl Peroxide Gel, 1.2%/5% in pediatric patients below the age of 12 have not been established.

8.5 Geriatric Use

Clinical studies of Clindamycin Phosphate and Benzoyl Peroxide Gel, 1.2%/5% did not include sufficient numbers of subjects ages 65 and over to determine whether they respond differently from younger subjects.

11 DESCRIPTION

Clindamycin Phosphate and Benzoyl Peroxide Gel, 1.2%/5% is a fixed combination product with two active ingredients in a white to slightly yellow, opaque, aqueous gel formulation.

Clindamycin phosphate is a water soluble ester of the semi-synthetic antibiotic produced by a 7(S)-chloro-substitution of the 7(R)-hydroxyl group of the parent antibiotic lincomycin.

Clindamycin phosphate is C18H34ClN2O8PS. The structural formula for clindamycin phosphate is represented below:

Clindamycin phosphate has a molecular weight of 504.97 and its chemical name is methyl 7-chloro-6,7,8-trideoxy-6-(1-methyl-trans-4-propyl-L-2-pyrrolidinecarboxamido)-1-thio-L- threo-α-D-galacto-octopyranoside 2-(dihydrogen phosphate).

Benzoyl peroxide is C14H14O4. It has the following structural formula:

Benzoyl Peroxide has a molecular weight of 242.23.

Each gram of Clindamycin Phosphate and Benzoyl Peroxide Gel, 1.2%/5% contains 10 mg (1%) clindamycin, as clindamycin phosphate, and 50 mg (5%) benzoyl peroxide in a base consisting of carbomer homopolymer (type C), dimethicone, edetate disodium, glycerin, poloxamer 182, purified water, silicon dioxide, and sodium hydroxide.

12 CLINICAL PHARMACOLOGY

12.1 Mechanism of Action

Clindamycin

Clindamycin is a lincosamide antibacterial [see Clinical Pharmacology (12.4)].

Benzoyl Peroxide

Benzoyl peroxide is an oxidizing agent with bacteriocidal and keratolytic effects, but the precise mechanism of action is unknown.

12.3 Pharmacokinetics

A comparative trial of the pharmacokinetics of Clindamycin Phosphate and Benzoyl Peroxide Gel, 1.2%/5% and 1% clindamycin solution alone in 78 subjects indicated that mean plasma clindamycin levels during the 4-week dosing period were less than 0.5 ng per mL for both treatment groups.

Benzoyl peroxide has been shown to be absorbed by the skin where it is converted to benzoic acid.

Less than 2% of the dose enters systemic circulation as benzoic acid.

12.4 Microbiology

Clindamycin binds to the 50S ribosomal subunits of susceptible bacteria and prevents elongation of peptide chains by interfering with peptidyl transfer, thereby suppressing protein synthesis.

In Vivo Activity

No microbiology studies were conducted in the clinical trials with this product.

In Vitro Activity

The clindamycin and benzoyl peroxide components individually have been shown to have in vitro activity against Propionibacterium acnes, an organism which has been associated with acne vulgaris; however, the clinical significance of this in vitro activity is not known.

Drug Resistance

There are reports of an increase of P. acnes resistance to clindamycin in the treatment of acne. In patients with P. acnes resistant to clindamycin, the clindamycin component may provide no additional benefit beyond benzoyl peroxide alone.

13 NONCLINICAL TOXICOLOGY

13.1 Carcinogenesis, Mutagenesis, Impairment Of Fertility

Benzoyl peroxide has been shown to be a tumor promoter and progression agent in a number of animal studies. Benzoyl peroxide in acetone at doses of 5 and 10 mg administered twice per week induced squamous cell skin tumors in transgenic TgAC mice in a study using 20 weeks of topical treatment. The clinical significance of this is unknown.

In a 2-year dermal carcinogenicity study in mice, treatment with Clindamycin Phosphate and Benzoyl Peroxide Gel, 1.2%/5% at doses up to 8,000 mg per kg per day (16 times the highest recommended adult human dose of 2.5 g Clindamycin Phosphate and Benzoyl Peroxide Gel, 1.2%/5%, based on mg per m^2) did not cause an increase in skin tumors. However, topical treatment with another formulation containing 1% clindamycin and 5% benzoyl peroxide at doses of 100, 500, or 2,000 mg per kg per day caused a dose-dependent increase in the incidence of keratoacanthoma at the treated skin site of male rats in a 2-year dermal carcinogenicity study in rats.

In a 52-week photocarcinogenicity study in hairless mice (40 weeks of treatment followed by 12 weeks of observation), the median time to onset of skin tumor formation decreased and the number of tumors per mouse increased relative to controls following chronic concurrent topical treatment with Clindamycin Phosphate and Benzoyl Peroxide Gel, 1.2%/5% and exposure to ultraviolet radiation.

Genotoxicity studies were not conducted with Clindamycin Phosphate and Benzoyl Peroxide Gel, 1.2%/5%. Clindamycin phosphate was not genotoxic in Salmonella typhimurium or in a rat micronucleus test. Benzoyl peroxide has been found to cause DNA strand breaks in a variety of mammalian cell types, to be mutagenic in Salmonella typhimurium tests by some but not all investigators, and to cause sister chromatid exchanges in Chinese hamster ovary cells.

Studies have not been performed with Clindamycin Phosphate and Benzoyl Peroxide Gel, 1.2%/5% or benzoyl peroxide to evaluate the effect on fertility. Fertility studies in rats treated orally with up to 300 mg per kg per day of clindamycin (approximately 120 times the amount of clindamycin in the highest recommended adult human dose of 2.5 g Clindamycin Phosphate and Benzoyl Peroxide Gel, 1.2%/5%, based on mg per m^2) revealed no effects on fertility or mating ability.

14 CLINICAL STUDIES

In five randomized, double-blind clinical trials of 1,319 subjects, 397 used Clindamycin Phosphate and Benzoyl Peroxide Gel, 1.2%/5%, 396 used benzoyl peroxide, 349 used clindamycin, and 177 used vehicle. Subjects were instructed to wash the face, wait 10 to 20 minutes, and then apply medication to the entire face, once daily in the evening before retiring. Clindamycin Phosphate and Benzoyl Peroxide Gel, 1.2%/5% applied once daily for 11 weeks was significantly more effective than vehicle, benzoyl peroxide, and clindamycin in the treatment of inflammatory lesions of moderate to moderately severe facial acne vulgaris in three of the five trials (Trials 1, 2, and 5).
Subjects were evaluated and acne lesions counted at each clinical visit at Weeks 2, 5, 8, 11. The primary efficacy measures were the lesion counts and the investigator's global assessment evaluated at Week 11. Percent reductions in inflammatory lesion counts after treatment for 11 weeks in these 5 trials are shown in Table 2.
Table 2. Mean Percent Reduction in Inflammatory Lesion Counts

Treatment | Trial 1 (n = 120) | Trial 2 (n = 273) | Trial 3 (n = 280) | Trial 4 (n = 288) | Trial 5 (n = 358)
Clindamycin Phosphate and Benzoyl Peroxide Gel, 1.2%/5% | 65% | 56% | 42% | 57% | 52%
Benzoyl Peroxide | 36% | 37% | 32% | 57% | 41%
Clindamycin | 34% | 30% | 38% | 49% | 33%
Vehicle | 19% | -0.4% | 29% |  | 29%

The group treated with Clindamycin Phosphate and Benzoyl Peroxide Gel, 1.2%/5% showed greater overall improvement in the investigator's global assessment than the benzoyl peroxide, clindamycin, and vehicle groups in three of the five trials (Trials 1, 2, and 5).
Clinical trials have not adequately demonstrated the effectiveness of Clindamycin Phosphate and Benzoyl Peroxide Gel, 1.2%/5% versus benzoyl peroxide alone in the treatment of non-inflammatory lesions of acne.

16 HOW SUPPLIED/STORAGE AND HANDLING

16.1 How Supplied
Clindamycin Phosphate and Benzoyl Peroxide Gel, 1.2%/5% is a white to slightly yellow, opaque gel.

NDC: 71335-2878-1: 45 g in a TUBE

16.2 Storage and Handling
Pharmacist:

Prior to Dispensing: Store in a cold place, preferably in a refrigerator, between 2°C and 8°C (36°F and 46°F). Do not freeze.
16.3 Dispensing Instructions for the Pharmacist
Dispense Clindamycin Phosphate and Benzoyl Peroxide Gel, 1.2%/5% with a 60 day expiration date.
Specify “Store at room temperature up to 25°C (77°F). Do not freeze.”
Keep tube tightly closed.
Keep out of the reach of small children.

Repackaged/Relabeled by:
Bryant Ranch Prepack, Inc.
Burbank, CA 91504

17 PATIENT COUNSELING INFORMATION

Advise the patient to read the FDA-approved patient labeling (Patient Information).

- Patients who develop allergic reactions such as severe swelling or shortness of breath should discontinue use and contact their physician immediately.
- Clindamycin Phosphate and Benzoyl Peroxide Gel, 1.2%/5% may cause irritation such as erythema, scaling, itching, or burning, especially when used in combination with other topical acne therapies.
- Excessive or prolonged exposure to sunlight should be limited. To minimize exposure to sunlight, a hat or other clothing should be worn. Sunscreen may also be used.
- Clindamycin Phosphate and Benzoyl Peroxide Gel, 1.2%/5% may bleach hair or colored fabric.
- Clindamycin Phosphate and Benzoyl Peroxide Gel, 1.2%/5% may cause skin and facial hair to temporarily change color (yellow/orange) when used with topical sulfone products.

Manufactured by:

Encube Ethicals Pvt. Ltd.
Plot No. C-1, Madkaim Industrial Estate, Madkaim,
Post Mardol, Ponda, Goa-403 404, India.

Distributed by:

Encube Ethicals , Inc.
200 Meredith Avenue, Suite 101A
Durham, NC 27713 USA

PATIENT INFORMATION

PHARMACIST – DETACH HERE AND GIVE INSTRUCTIONS TO PATIENT

PATIENT INFORMATION

Clindamycin Phosphate and Benzoyl Peroxide Gel, 1.2%/5%

Important: For use on the skin only (topical use). Do not get Clindamycin Phosphate and Benzoyl Peroxide Gel, 1.2%/5% in your mouth, eyes, vagina or on your lips.

Read this Patient Information before you start using Clindamycin Phosphate and Benzoyl Peroxide Gel, 1.2%/5% and each time you get a refill. There may be new information. This information does not take the place of talking with your healthcare provider about your medical condition or your treatment.

What is Clindamycin Phosphate and Benzoyl Peroxide Gel, 1.2%/5%?

Clindamycin Phosphate and Benzoyl Peroxide Gel, 1.2%/5% is a prescription medicine used on the skin (topical) to treat inflamed acne in people 12 years and older.

Who should not use Clindamycin Phosphate and Benzoyl Peroxide Gel, 1.2%/5%?

Do not use Clindamycin Phosphate and Benzoyl Peroxide Gel, 1.2%/5% if you have:

- had an allergic reaction to clindamycin, lincomycin, benzoyl peroxide, or any of the ingredients in Clindamycin Phosphate and Benzoyl Peroxide Gel, 1.2%/5%. See the end of this leaflet for a complete list of ingredients in Clindamycin Phosphate and Benzoyl Peroxide Gel, 1.2%/5%.
- Crohn's disease or ulcerative colitis.
- had inflammation of the colon (colitis) with past antibiotic use.

What should I tell my healthcare provider before using Clindamycin Phosphate and Benzoyl Peroxide Gel, 1.2%/5%?

Before using Clindamycin Phosphate and Benzoyl Peroxide Gel, 1.2%/5%, tell your healthcare provider about all of your medical conditions, including if you:

- plan to have surgery with general anesthesia.
- are sensitive to sunlight.
- are pregnant or plan to become pregnant.It is not known if Clindamycin Phosphate and Benzoyl Peroxide Gel, 1.2%/5% will harm your unborn baby.
- are breastfeeding or plan to breastfeed. It is not known if Clindamycin Phosphate and Benzoyl Peroxide Gel, 1.2%/5% passes into your breast milk. One of the medicines in Clindamycin Phosphate and Benzoyl Peroxide Gel, 1.2%/5% is clindamycin. Clindamycin when taken by mouth or by injection has been reported to appear in breast milk. You and your healthcare provider should decide if you will use Clindamycin Phosphate and Benzoyl Peroxide Gel, 1.2%/5% while breastfeeding.

Tell your healthcare provider about all the medicines you take, including prescription or over-the-counter medicines, vitamins, herbal supplements, and skin products you use. Using other topical acne products may increase the irritation of your skin when used with Clindamycin Phosphate and Benzoyl Peroxide Gel, 1.2%/5%.

- Especially tell your healthcare provider if you take a medicine that contains erythromycin. Clindamycin Phosphate and Benzoyl Peroxide Gel, 1.2%/5% should not be used with products that contain erythromycin.
- Clindamycin Phosphate and Benzoyl Peroxide Gel, 1.2%/5% may cause skin and facial hair to temporarily change color (yellow or orange) when used with topical products that contain sulfones.

How should I use Clindamycin Phosphate and Benzoyl Peroxide Gel, 1.2%/5%?

- Use Clindamycin Phosphate and Benzoyl Peroxide Gel, 1.2%/5% exactly as your healthcare provider tells you to use it.
- Before you apply Clindamycin Phosphate and Benzoyl Peroxide Gel, 1.2%/5%, wash your face gently with a mild soap, rinse with warm water, and pat the skin dry.
- Apply a thin layer of Clindamycin Phosphate and Benzoyl Peroxide Gel, 1.2%/5% to your face 1 time a day, in the evening or as directed by your healthcare provider. Wash your hands with soap and water after applying Clindamycin Phosphate and Benzoyl Peroxide Gel, 1.2%/5%.
- Do not get Clindamycin Phosphate and Benzoyl Peroxide Gel, 1.2%/5% in your mouth, eyes, nose, vagina, or on your lips. Do not get Clindamycin Phosphate and Benzoyl Peroxide Gel, 1.2%/5% on cuts or open wounds.

What should I avoid while using Clindamycin Phosphate and Benzoyl Peroxide Gel, 1.2%/5%?

- Limit your time in sunlight. Avoid using tanning beds or sun lamps. If you have to be in sunlight, wear a wide-brimmed hat or other protective clothing. Sunscreen may also be used.
- Talk to your healthcare provider if you spend a lot of time in the sun.
- Clindamycin Phosphate and Benzoyl Peroxide Gel, 1.2%/5% may bleach hair or colored fabric.

What are the possible side effects with Clindamycin Phosphate and Benzoyl Peroxide Gel, 1.2%/5%?

Clindamycin Phosphate and Benzoyl Peroxide Gel, 1.2%/5% may cause serious side effects, including:

- Inflammation of the colon (colitis). Stop using Clindamycin Phosphate and Benzoyl Peroxide Gel, 1.2%/5% and call your healthcare provider right away if you have severe watery diarrhea, or bloody diarrhea.
- Allergic reactions. Stop using Clindamycin Phosphate and Benzoyl Peroxide Gel, 1.2%/5% and call your healthcare provider or get help right away if you have any of the following symptoms:

o severe itching

o swelling of your face, eyes, lips, tongue, or throat

o trouble breathing

The most common side effects with Clindamycin Phosphate and Benzoyl Peroxide Gel, 1.2%/5% are skin reactions and may include redness, peeling, dryness, and burning. These are not all the possible side effects with Clindamycin Phosphate and Benzoyl Peroxide Gel, 1.2%/5%.

Call your doctor for medical advice about side effects. You may report side effects to FDA at 1-800- FDA-1088.

How should I store Clindamycin Phosphate and Benzoyl Peroxide Gel, 1.2%/5%?

- Store Clindamycin Phosphate and Benzoyl Peroxide Gel, 1.2%/5% at room temperature up to 25°C (77°F). Do not freeze Clindamycin Phosphate and Benzoyl Peroxide Gel, 1.2%/5%.
- The expiration date of Clindamycin Phosphate and Benzoyl Peroxide Gel, 1.2%/5% is 60 days from the date when you fill your prescription.
- Safely throw away expired Clindamycin Phosphate and Benzoyl Peroxide Gel, 1.2%/5%.
- Keep the tube tightly closed.

Keep Clindamycin Phosphate and Benzoyl Peroxide Gel, 1.2%/5% and all medicines out of the reach of children.

General information about Clindamycin Phosphate and Benzoyl Peroxide Gel, 1.2%/5%

Medicines are sometimes prescribed for purposes other than those listed in a Patient Information leaflet. Do not use Clindamycin Phosphate and Benzoyl Peroxide Gel, 1.2%/5% for a condition for which it was not prescribed. Do not give Clindamycin Phosphate and Benzoyl PeroxideGel, 1.2%/5% to other people, even if they have the same symptoms you have. It may harm them.

If you would like more information, talk with your healthcare provider. You can also ask your pharmacist or healthcare provider for information about Clindamycin Phosphate and Benzoyl Peroxide Gel, 1.2%/5% that is written for health professionals.

For more information, call 1-833-285-4151.

What are the ingredients in Clindamycin Phosphate and Benzoyl Peroxide Gel, 1.2%/5%?

Active ingredients: clindamycin phosphate 1.2% and benzoyl peroxide 5%

Inactive ingredients: carbomer homopolymer (type C), dimethicone, edetate disodium, glycerin, poloxamer 182, purified water, silicon dioxide, and sodium hydroxide.

This Patient Information has been approved by the U.S. Food and Drug Administration.

Manufactured by:

Encube Ethicals Pvt. Ltd.
Plot No. C-1, Madkaim Industrial Estate, Madkaim,
Post Mardol, Ponda, Goa-403 404, India.

Distributed by:

Encube Ethicals , Inc.
200 Meredith Avenue, Suite 101A
Durham, NC 27713 USA

Rev: 01

July 2020

PACKAGE LABEL

Benzoyl/Clindamycin 1.2% / 5% Gel #45